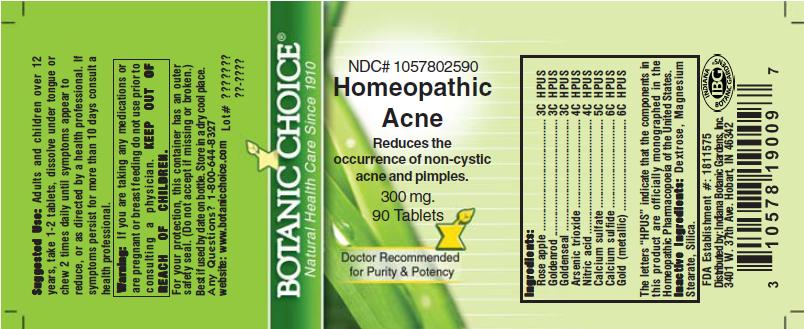 DRUG LABEL: Homeopathic Acne Formula
NDC: 10578-025 | Form: TABLET
Manufacturer: Indiana Botanic Gardens
Category: homeopathic | Type: HUMAN OTC DRUG LABEL
Date: 20110325

ACTIVE INGREDIENTS: ARSENIC TRIOXIDE 4 [hp_C]/1 1; NITRIC ACID 4 [hp_C]/1 1; CALCIUM SULFIDE 6 [hp_C]/1 1; SYZYGIUM JAMBOS SEED 3 [hp_C]/1 1; GOLD 6 [hp_C]/1 1; CALCIUM SULFATE ANHYDROUS 5 [hp_C]/1 1; SOLIDAGO VIRGAUREA FLOWERING TOP 3 [hp_C]/1 1; GOLDENSEAL 3 [hp_C]/1 1
INACTIVE INGREDIENTS: DEXTROSE; MAGNESIUM STEARATE ; SILICON DIOXIDE 

Homeopathic Acne Formula

ACTIVE INGREDIENT

I n g r e d i e n t s :
Rose apple ........................ 3C HPUS
Goldenrod ..................... 3C HPUS
Goldenseal ................. 3C HPUS
Arsenic trioxide ....................... 4C HPUS
Nitric acid ........................ 4C HPUS
Calcium sulfate ................... 5C HPUS
Calcium sulfide ......... 6C HPUS
Gold (metallic) ..................... 6C HPUS

The letters “HPUS” indicate that the components in
this product are officially monographed in the
Homeopathic Pharmacopoeia of the United States.

PURPOSE

Reduces the
occurrence of non-cystic
acne and pimples.

KEEP OUT OF
REACH OF CHILDREN.

INDICATIONS AND USAGE

Reduces the
occurrence of non-cystic
acne and pimples.

WARNINGS

Warning: If you are taking any medications or
are pregnant or breast feeding do not use prior to
consulting a physician.

DOSAGE AND ADMINISTRATION

Suggested Use: Adults and children over 12
years, take 1-2 tablets, dissolve under tongue or
chew 2 times daily until symptoms appear to
reduce, or as directed by a health professional. If
symptoms persist for more than 10 days consult a
health professional.

Inactive Ingredients: Dextrose, Magnesium
Stearate, Silica.

PACKAGE LABEL

NDC# 1057802590

Homeopathic
Acne
Reduces the
occurrence of non-cystic
acne and pimples.
300 mg.
90 Tablets

USER SAFETY WARNINGS

For your protection, this container has an outer
safety seal. (Do not accept if missing or broken.)
Best if used by date on bottle. Store in a dry cool place.
Any Questions? 1-800-644-8327
website: www.botanicchoice.com

FDA Establishment #: 1811575

Distributed by: Indiana Botanic Gardens, Inc.
3401 W. 37th Ave. Hobart, IN 46342